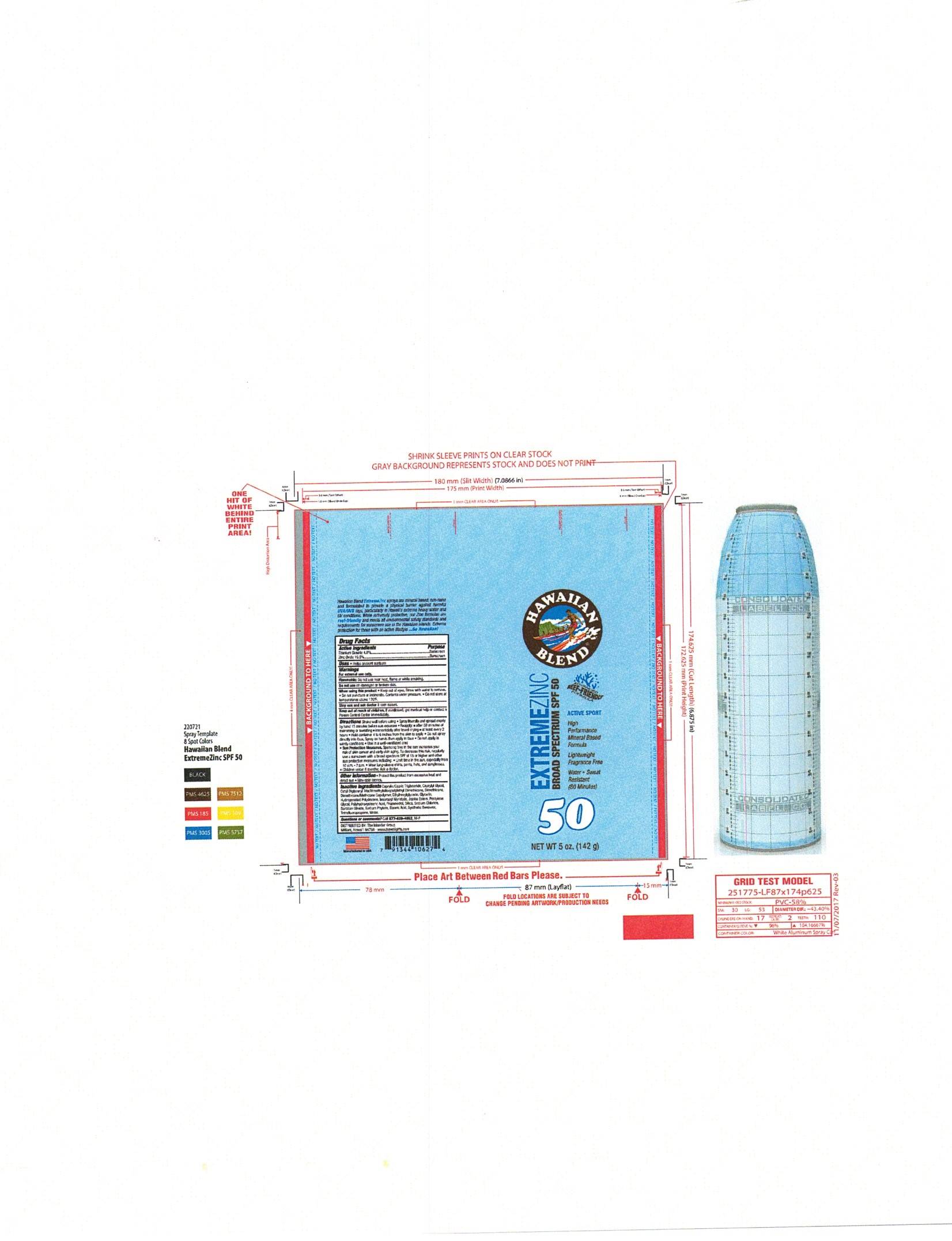 DRUG LABEL: Hawaiian Blend Extreme Zinc SPF 50
NDC: 87313-004 | Form: AEROSOL
Manufacturer: The Islander Group
Category: otc | Type: HUMAN OTC DRUG LABEL
Date: 20260107

ACTIVE INGREDIENTS: TITANIUM DIOXIDE 4 g/100 g; ZINC OXIDE 19.5 g/100 g
INACTIVE INGREDIENTS: PENTYLENE GLYCOL; MEDIUM-CHAIN TRIGLYCERIDES; JOJOBA OIL, RANDOMIZED; SODIUM CHLORIDE; CAPRYLYL GLYCOL; CETYL DIGLYCERYL TRIS(TRIMETHYLSILOXY)SILYLETHYL DIMETHICONE (3500 MM2/S); ETHYLHEXYLGLYCERIN; HYDROGENATED POLYDECENE TYPE I; SILICON DIOXIDE; STEARIC ACID; WATER; SORBITAN OLIVATE; SYNTHETIC BEESWAX; POLYHYDROXYSTEARIC ACID STEARATE; GLYCERIN; 2,3,5,6-TETRAFLUOROPHENOL; PROPANEDIOL; DIMETHICONE; HYDROGEN DIMETHICONE (13 CST); PHYTATE SODIUM; ISOPROPYL MYRISTATE

Hawaiian Blend Extreme Zinc Broad Spectrum SPF 50 Sunscreen Spray

Active Ingredient

Zinc Oxide

Titanium Dioxide

PURPOSE

Zinc Oxide - 19.5% ................. Sunscreen

Titanium Dioxide – 4.0%.................. Sunscreen

WARNINGS

For external use only

Do not use on damaged or broken skin

when using this product keep out of eyes-rinse with water to remove.

Stop use and ask a doctor if rash occurs.

Keep out of reach of children.If swallowed, get medical help or contact a Poison Control Center right away.

DOSAGE AND ADMINISTRATION

Apply liberally 15 minutews befor sun exposure

Reaaply:

- after 80 monutes of swimming or sweating

- immediatly after towel drying

- at least every 2 hours

INDICATIONS AND USAGE

Helps prevent sunburn

Higher SPF gives more sunburn protection

If used as directed with other sun protection measures, decreases the reisk of skin cancer and early skim agingcaused by the s

INACTIVE INGREDIENT

Caprylic/Capric Triglyceride

Caprylyl Glycol

Cetyl Diglyceryl Tris(Trimethylsiloxy)silylethyl Dimethicone

Dimethicone

Dimethicone/Methicone Copolymer

Sodium Phytate

Ethylhexylglycerin

Glycerin

Hydrogenated Polydecene

Isopropyl Myristate

Jojoba Esters

Pentylene Glycol

Polyhydroxystearic Acid

Propanediol

Silica

Sodium Chloride

Sorbitan Olivate

Stearic Acid

Synthetic Beeswax

Tetrafluoropropene

Fragrance

Water